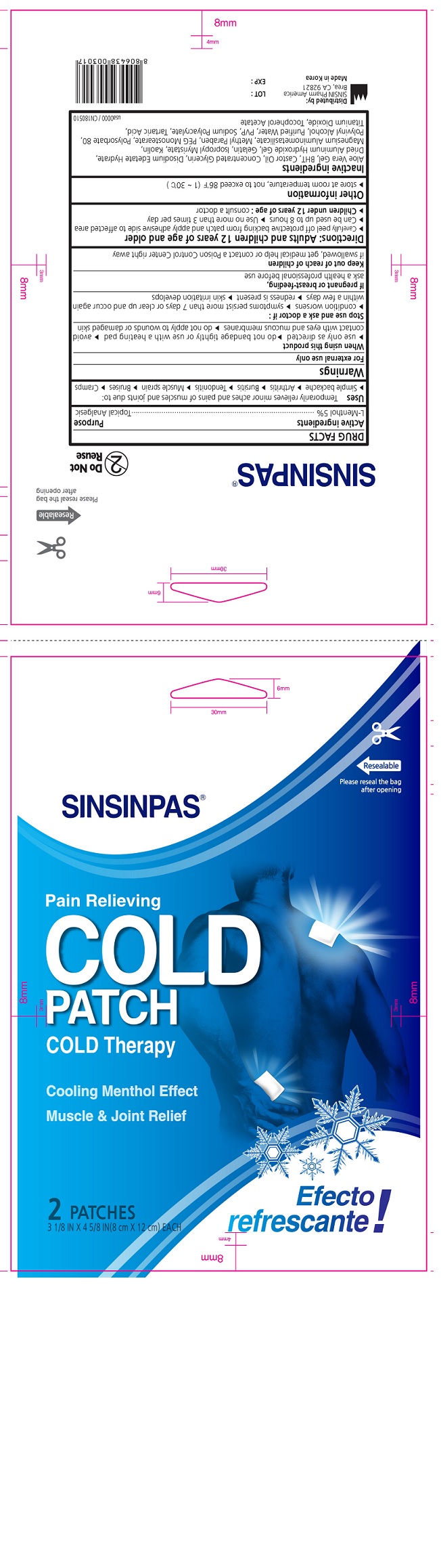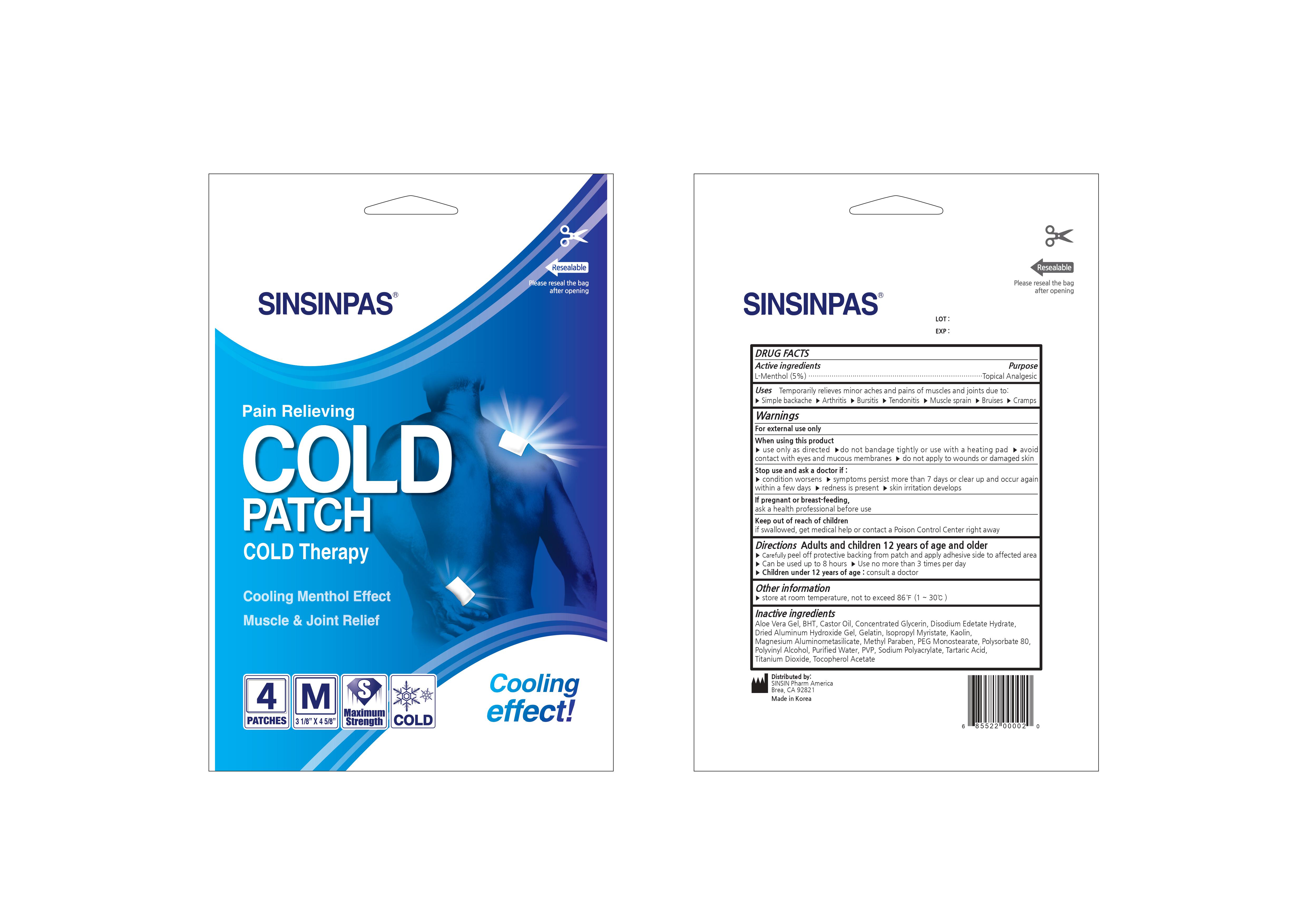 DRUG LABEL: SINSINPAS COLD
NDC: 55264-104 | Form: PATCH
Manufacturer: Sinsin Pharmaceutical Co., Ltd.
Category: otc | Type: HUMAN OTC DRUG LABEL
Date: 20240105

ACTIVE INGREDIENTS: MENTHOL 0.85 g/17 g
INACTIVE INGREDIENTS: SODIUM POLYACRYLATE (8000 MW); POVIDONE; METHYLPARABEN; GELATIN; GLYCERYL MONOSTEARATE; TARTARIC ACID; TITANIUM DIOXIDE; .ALPHA.-TOCOPHEROL ACETATE; SILODRATE; BUTYLATED HYDROXYTOLUENE; POLYSORBATE 80; CASTOR OIL; ALOE VERA LEAF; EDETATE DISODIUM; ALUMINUM HYDROXIDE; ISOPROPYL MYRISTATE; WATER; GLYCERIN; KAOLIN; POLYVINYL ALCOHOL, UNSPECIFIED

SINSINPAS COLD PATCH

Active Ingredients

L-Menthol (5%)

Purpose

Topical Analgesic

Keep out of reach of children. If swallowed, get medical help or contact a Poison Control Center (1-800-222-1222) right away.

Uses

For the temporarily relief of minor aches and pains of muscles and joints associated with:

- Arthritis
- Simple backache
- Strains
- Bruises
- Sprains

Warnings

For external use only

Do not use

- on wounds or damaged skin
- if you are allergic to any ingredients of this product
- with a heating pad
- with, or at the same time as, other external analgesic products

When using this product

- do not use otherwise than directed
- avoid contact with eyes, mucous membranes or rashes
- do not bandage tightly

Ask a doctor before use if you are prone to allergic reaction from aspirin or salicylates

Stop use and ask a doctor if

- rash, itching, or excessive skin irritation develops
- conditions worsen
- symptoms persist for more than 7 days
- symptoms clear up and occur again within a few days

If pregnant or breast-feeding, ask a health professional before use.

Directions

Adults and children 12 years of age and over:

- Clean and dry affected area
- Remove patch from film
- Apply to affected area no more than 3 to 4 times daily for 7 days
- Remove patch from skin after at most 8 hours’ application

Children undress 12 years of age: consult a doctor

Inactive Ingredients

Aloe vera gel, BHT, Castor oil, concentrated glycerin, disodium edetate hydrate, dried aluminum hydoxide gel, gelatin, isopropyl myristate, kaolin, magnesium aluminometasilicate, methyl paraben, PEG monostearte, polysorbate 80, polyvinyl alcohol, purified water, PVP, sodium polyacrylate, tartaric acid, titanium dioxide, tocopherol acetate.